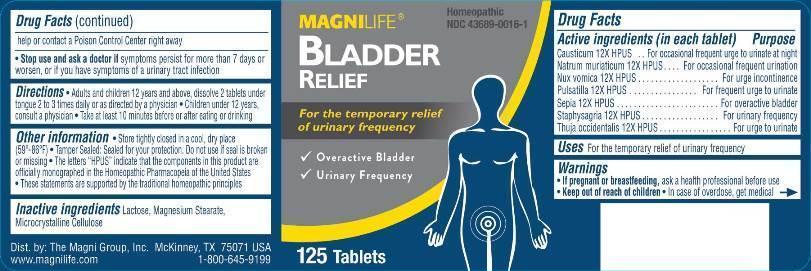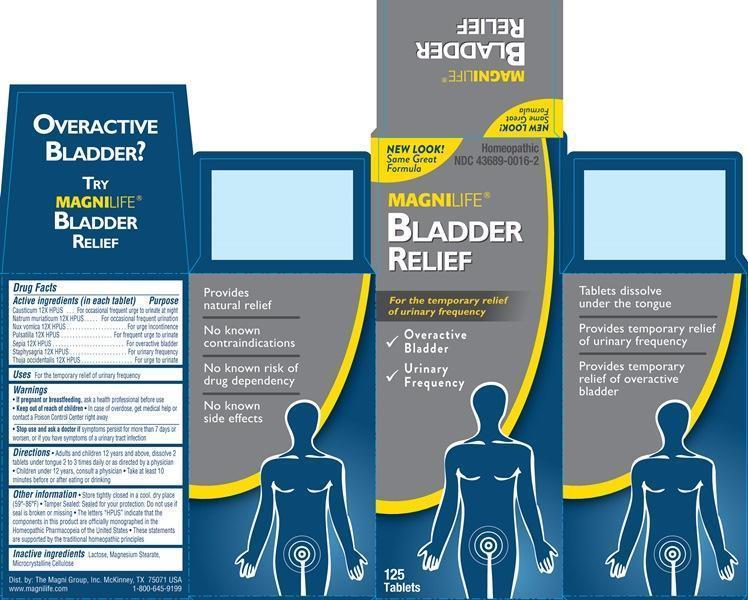 DRUG LABEL: Bladder Relief
NDC: 43689-0016 | Form: TABLET
Manufacturer: Magni Company
Category: homeopathic | Type: HUMAN OTC DRUG LABEL
Date: 20241105

ACTIVE INGREDIENTS: CAUSTICUM 12 [hp_X]/1 1; SODIUM CHLORIDE 12 [hp_X]/1 1; STRYCHNOS NUX-VOMICA SEED 12 [hp_X]/1 1; PULSATILLA VULGARIS WHOLE 12 [hp_X]/1 1; SEPIA OFFICINALIS JUICE 12 [hp_X]/1 1; DELPHINIUM STAPHISAGRIA SEED 12 [hp_X]/1 1; THUJA OCCIDENTALIS LEAFY TWIG 12 [hp_X]/1 1
INACTIVE INGREDIENTS: LACTOSE; MAGNESIUM STEARATE; CELLULOSE, MICROCRYSTALLINE

DRUG FACTS:

ACTIVE INGREDIENTS:

Causticum 12X, Natrum Muriaticum 12X, Nux Vomica 12X, Pulsatilla 12X, Sepia 12X, Staphysagria 12X, Thuja Occidentalis 12X

USES:

For the temporary relief of urinary frequency

WARNINGS:

• If pregnant or breastfeeding, ask a health professional before use

• Keep out of reach of children

• In case of overdose, get medical help or contact a Poison Control Center right away

• Stop use and ask a doctor if symptoms persist for more than 7 days or worsen, or if you have symptoms of a urinary tract infection

OTHER INFORMATION:

• Store tightly closed in a cool, dry place (59° - 86°F)

• Tamper sealed: Sealed for your protection. Do not use if seal is broken or missing

• The letters "HPUS" indicate that the components in this product are officially monographed in the Homeopathic Pharmacopeia of the United

States

• These statements are supported by the traditional homeopathic principles

Keep out of reach of children. In case of overdose, get medical help or contact a Poison Control Center right away

DIRECTIONS:

• Adults and children 12 years and above: Dissolve 2 tablets under tongue 2 to 3 times daily or as directed by a physician

• Children under 12: Consult a physician

• Take at least 10 minutes before or after eating or drinking

INACTIVE INGREDIENTS:

Lactose, Magnesium Stearate, Microcrystalline Cellulose

INDICATIONS:

For the temporary relief of urinary frequency

QUESTIONS:

Dist. by: The Magni Group, Inc. McKinney, TX 75071 USA

www.magilife.com 1-800-645-9199

PACKAGE LABEL DISPLAY:

MAGNILIFE Homeopathic

BLADDER NDC 43689-0016-1

RELIEF

For the temporary relief

of urinary frequency

√ Overactive Bladder

√ Urinary Frequency

125 Tablets